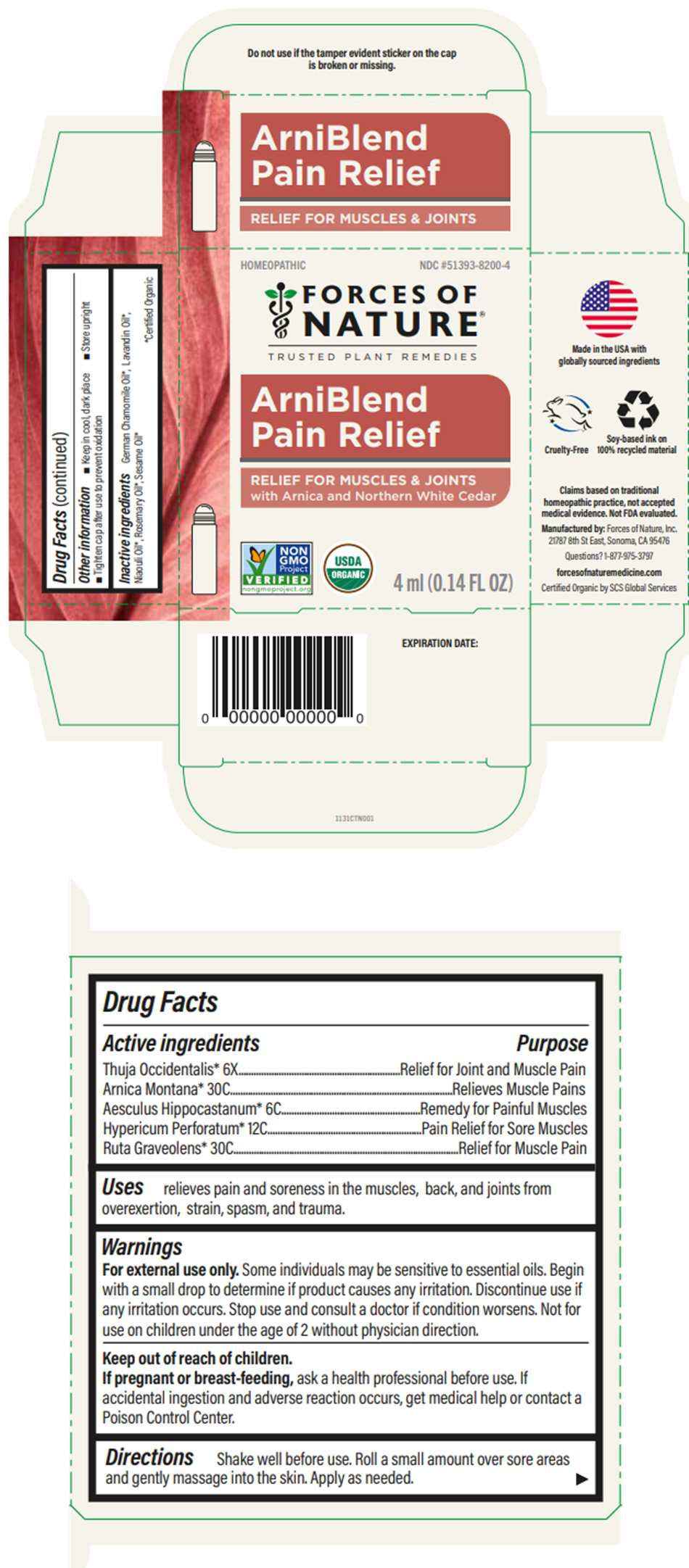 DRUG LABEL: Arniblend Pain Relief
NDC: 51393-8200 | Form: SOLUTION/ DROPS
Manufacturer: Forces of Nature
Category: homeopathic | Type: HUMAN OTC DRUG LABEL
Date: 20251006

ACTIVE INGREDIENTS: ARNICA MONTANA WHOLE 30 [hp_C]/100 mL; HORSE CHESTNUT 6 [hp_C]/100 mL; HYPERICUM PERFORATUM WHOLE 12 [hp_C]/100 mL; RUTA GRAVEOLENS FLOWERING TOP 30 [hp_C]/100 mL; THUJA OCCIDENTALIS LEAFY TWIG 6 [hp_X]/100 mL
INACTIVE INGREDIENTS: Sesame Oil; Lavandin Oil; CHAMOMILE FLOWER OIL; MELALEUCA QUINQUENERVIA LEAF OIL; Rosemary Oil

Arniblend Pain Relief

Drug Facts

ACTIVE INGREDIENT

Active ingredients | Purpose
Thuja Occidentalis 6X | Relief for Joint and Muscle Pain
Arnica Montana 30C | Relieves Muscle Pains
Aesculus Hippocastanum 6C | Remedy for Painful Muscles
Hypericum Perforatum 12C | Pain Relief for Sore Muscles
Ruta Graveolens 30C | Relief for Muscle Pain

Uses

relieves pain and soreness in the muscles, back, and joints from overexertion, strain, spasm, and trauma.

Warnings

For external use only. Some individuals may be sensitive to essential oils. Begin with a small drop to determine if product causes any irritation. Discontinue use if any irritation occurs. Stop use and consult a doctor if condition worsens. Not for use on children under the age of 2 without physician direction.

Keep out of reach of children.

PREGNANCY OR BREAST FEEDING

If pregnant or breast-feeding, ask a health professional before use. If accidental ingestion and adverse reaction occurs, get medical help or contact a Poison Control Center.

Directions

Shake well before use. Roll a small amount over sor areas and gently massage into the skin. Apply as needed.

Other information

- Keep in cool, dark place
- Store upright
- Tighten cap after use to prevent oxidation

Inactive ingredients

German Chamomile Oil [Certified Organic] , Lavandin Oil, Niaouli Oil, Rosemary Oil, Sesame Oil

Questions? 1-877-975-3797

Manufactured by: Forces of Nature, Inc.
21787 8th St East, Sonoma, CA 95476

PRINCIPAL DISPLAY PANEL - 4 ml Bottle Carton

HOMEOPATHIC

NDC #51393-8200-4

FORCES OF
NATURE®
TRUSTED PLANT REMEDIES

ArniBlend
Pain Relief

RELIEF FOR MUSCLES & JOINTS
with Arnica and Northern White Cedar

NON
GMO
Project
VERIFIED
nongmoproject.org

USDA
ORGANIC

4 ml (0.14 FL OZ)